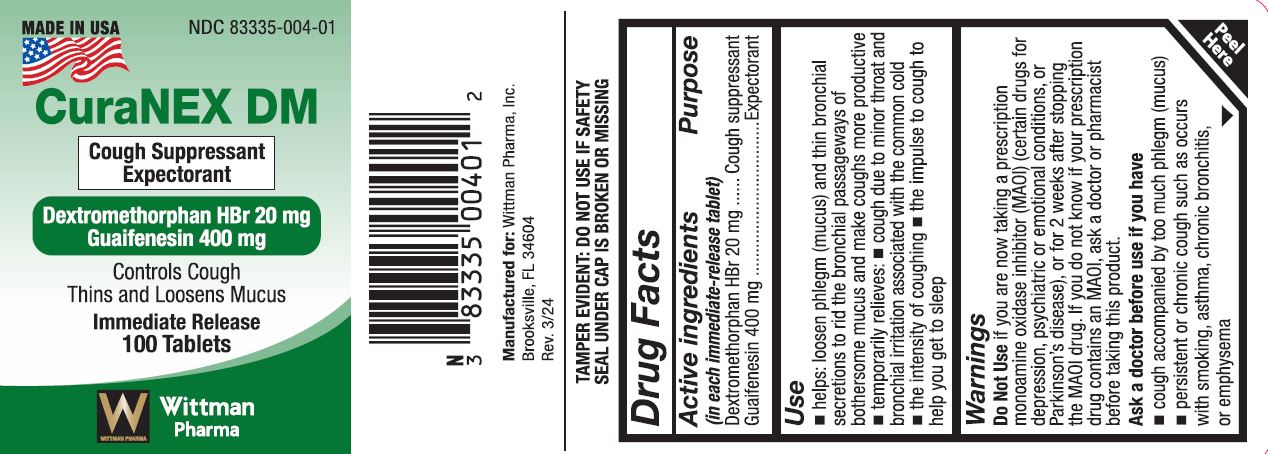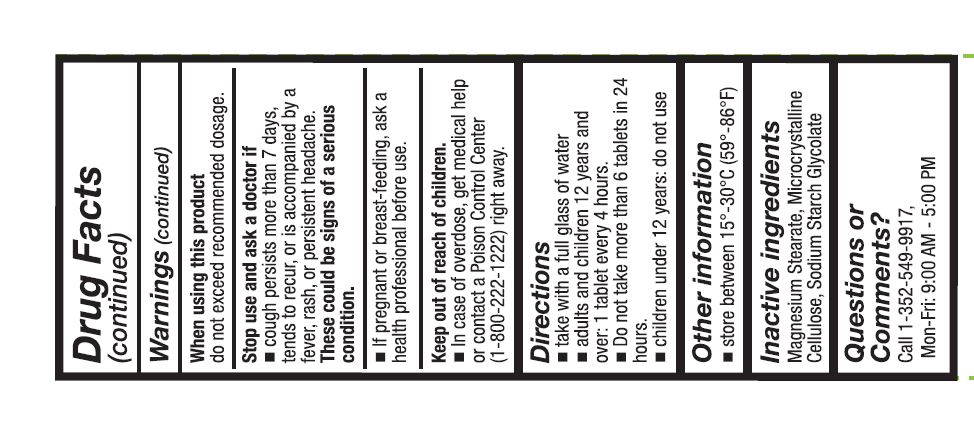 DRUG LABEL: CuraNEX DM
NDC: 83335-004 | Form: TABLET
Manufacturer: Wittman Pharma, Inc.
Category: otc | Type: HUMAN OTC DRUG LABEL
Date: 20240404

ACTIVE INGREDIENTS: GUAIFENESIN 400 mg/1 1; DEXTROMETHORPHAN 20 mg/1 1
INACTIVE INGREDIENTS: CELLULOSE, MICROCRYSTALLINE; SODIUM STARCH GLYCOLATE TYPE A; MAGNESIUM STEARATE

CuraNEX DM

DOSAGE AND ADMINISTRATION

■ take with a full glass of water

■ adults and children 12 years and over: 1 tablet

every 4 hours.

■ Do not take more than 6 tablets in 24 hours.

■ children under 12 years: do not use

Other information

Do Not Use ~ you are now taking a prescription

monoamine oxidase inhibitor (MAOI) (certain drugs for

depression, psychiatric or emotional conditions, or

Parkinson's disease), or for 2 weeks after stopping

the MAOI drug. If you do not know if your prescription

drug contains an MAOI, ask a doctor or pharmacist

before taking this product.

Ask a doctor before use If you have

■ cough accompanied by too much phlegm (mucus)

■ persistent or chronic cough such as occurs~~

with smoking, asthma, chronic bronchitis,

or emphysema

■When using this product

do not exceed recommended dosage.

Stop use and ask a doctor if

■ cough persists more than 7 days, tends to recur,

or is accompanied by a fever, rash, or persistent

headache.

These could be signs of a serious condition.

■ if pregnant or breast-feeding, ask a health

professional before use.

INACTIVE INGREDIENT

Magnesium Stearate, Microcrystalline Cellulose,

Sodium Starch Glycolate

INDICATIONS AND USAGE

Cough Suppressant and Expectorant

■ helps: loosen phlegm (mucus) and thin bronchial

secretions to rid the bronchial passageways of

bothersome mucus and make coughs more productive

■ temporarily relieves: ■ cough due to minor throat and

bronchial irritation associated with the common cold

■ the intensity of coughing ■ the impulse to cough to

help you get to sleep

Keep out of reach of children.

■ In case of overdose, get medical help or contact

a Poison Control Center (1-800-222-1222) right

away.

Purpose

(In each Immediate-re/ease tablet)

Dextromethorphan HBr 20 mg ...... Cough suppressant

Guaifenesin 400 mg ................................. Expectorant

ACTIVE INGREDIENT

Dextromethorphan HBr 20 mg ...... Cough suppressant

Guaifenesin 400 mg ................................. Expectorant

Drug Facts

Active ingredients Purpose

(In each Immediate-re/ease tablet)

Dextromethorphan HBr 20 mg ...... Cough suppressant

Guaifenesin 400 mg ................................. Expectorant

Use

■ helps: loosen phlegm (mucus) and thin bronchial

secretions to rid the bronchial passageways of

bothersome mucus and make coughs more productive

■ temporarily relieves: ■ cough due to minor throat and

bronchial irritation associated with the common cold

■ the intensity of coughing ■ the impulse to cough to

help you get to sleep

Warnings

Do Not Use ~ you are now taking a prescription

monoamine oxidase inhibitor (MAOI) (certain drugs for

depression, psychiatric or emotional conditions, or

Parkinson's disease), or for 2 weeks after stopping

the MAOI drug. If you do not know if your prescription

drug contains an MAOI, ask a doctor or pharmacist

before taking this product.

Ask a doctor before use If you have

■ cough accompanied by too much phlegm (mucus)

■ persistent or chronic cough such as occurs~~

with smoking, asthma, chronic bronchitis,

or emphysema

(Panel 2)

Warnings (continued)

When using this product

do not exceed recommended dosage.

Stop use and ask a doctor if

■ cough persists more than 7 days, tends to recur,

or is accompanied by a fever, rash, or persistent

headache.

These could be signs of a serious condition.

■ if pregnant or breast-feeding, ask a health

professional before use.

Keep out of reach of children.

■ In case of overdose, get medical help or contact

a Poison Control Center (1-800-222-1222) right

away.

Directions

■ take with a full glass of water

■ adults and children 12 years and over: 1 tablet

every 4 hours.

■ Do not take more than 6 tablets in 24 hours.

■ children under 12 years: do not use

Other information

■ store between 15°-30°C (59°-86°F)

Inactive ingredients

Magnesium Stearate, Microcrystalline Cellulose,

Sodium Starch Glycolate

Questions or Comments?

call 1-352-549-9917, Mon-Fri: 9:00AM - 5:00 PM